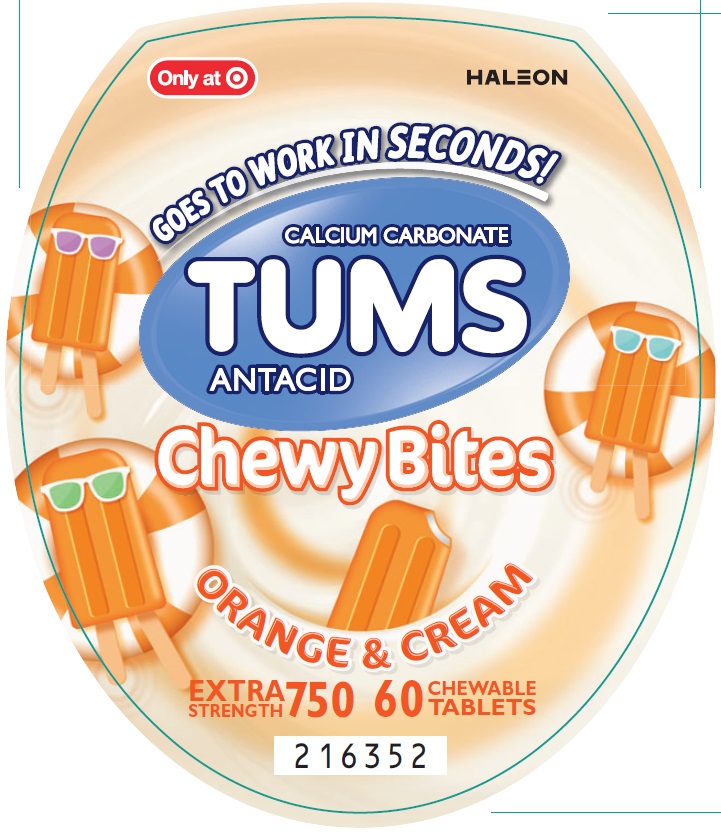 DRUG LABEL: Tums Chewy Bites
NDC: 0135-0642 | Form: TABLET, CHEWABLE
Manufacturer: Haleon US Holdings LLC
Category: otc | Type: HUMAN OTC DRUG LABEL
Date: 20250214

ACTIVE INGREDIENTS: CALCIUM CARBONATE 750 mg/1 1
INACTIVE INGREDIENTS: ACACIA; YELLOW WAX; CARNAUBA WAX; CITRIC ACID MONOHYDRATE; COCONUT OIL; STARCH, CORN; CORN SYRUP; DEXTRIN, CORN; FD&C YELLOW NO. 6; FD&C YELLOW NO. 6 ALUMINUM LAKE; MALTODEXTRIN; METHYLPARABEN; PHOSPHORIC ACID; PROPYLENE GLYCOL; PROPYLPARABEN; WATER; SHELLAC; SORBIC ACID; SORBITOL; SOYBEAN LECITHIN; SUCROSE; TITANIUM DIOXIDE; CORN OIL

Drug Facts

Active ingredient (per tablet)

Calcium carbonate 750 mg

Purpose

Antacid

Uses

relieves

- heartburn
- acid indigestion
- sour stomach
- upset stomach associated with these symptoms

Warnings

Ask a doctor or pharmacist before use if you are

presently taking a prescription drug. Antacids may interact with certain prescription drugs.

When using this product

- do not take more than 6 tablets in 24 hours
- if pregnant do not take more than 6 tablets in 24 hours
- do not use the maximum dosage for more than 2 weeks, except under the advice and supervision of a doctor

Directions

- adults and children 12 years of age and over: chew 2-4 tablets as symptoms occur, or as directed by a doctor. Chew or crush tablets completely before swallowing.
- do not take for symptoms that persist for more than 2 weeks unless advised by a doctor

Other Information

- each chewable tablet contains: elemental calcium 300 mg
- do not store above 25°C (77°F)

Inactive ingredients

acacia, beeswax, carnauba wax, citric acid, coconut oil, corn starch, corn syrup, dextrin, FD&C yellow no. 6, FD&C yellow no. 6 aluminum lake, maltodextrin, methylparaben, natural and artificial flavors, pharmaceutical ink, phosphoric acid, propylene glycol, propylparaben, purified water, shellac, sorbic acid, sorbitol, soy lecithin, sucrose, titanium dioxide, vegetable oil

Questions or comments?

1-800-452-0051

Principal Display Panel

GOES TO WORK IN SECONDS!

CALCIUM CARBONATE

TUMS

ANTACID

Chewy Bites

ORANGE & CREAM

EXTRA STRENGTH 750

60 CHEWABLE TABLETS